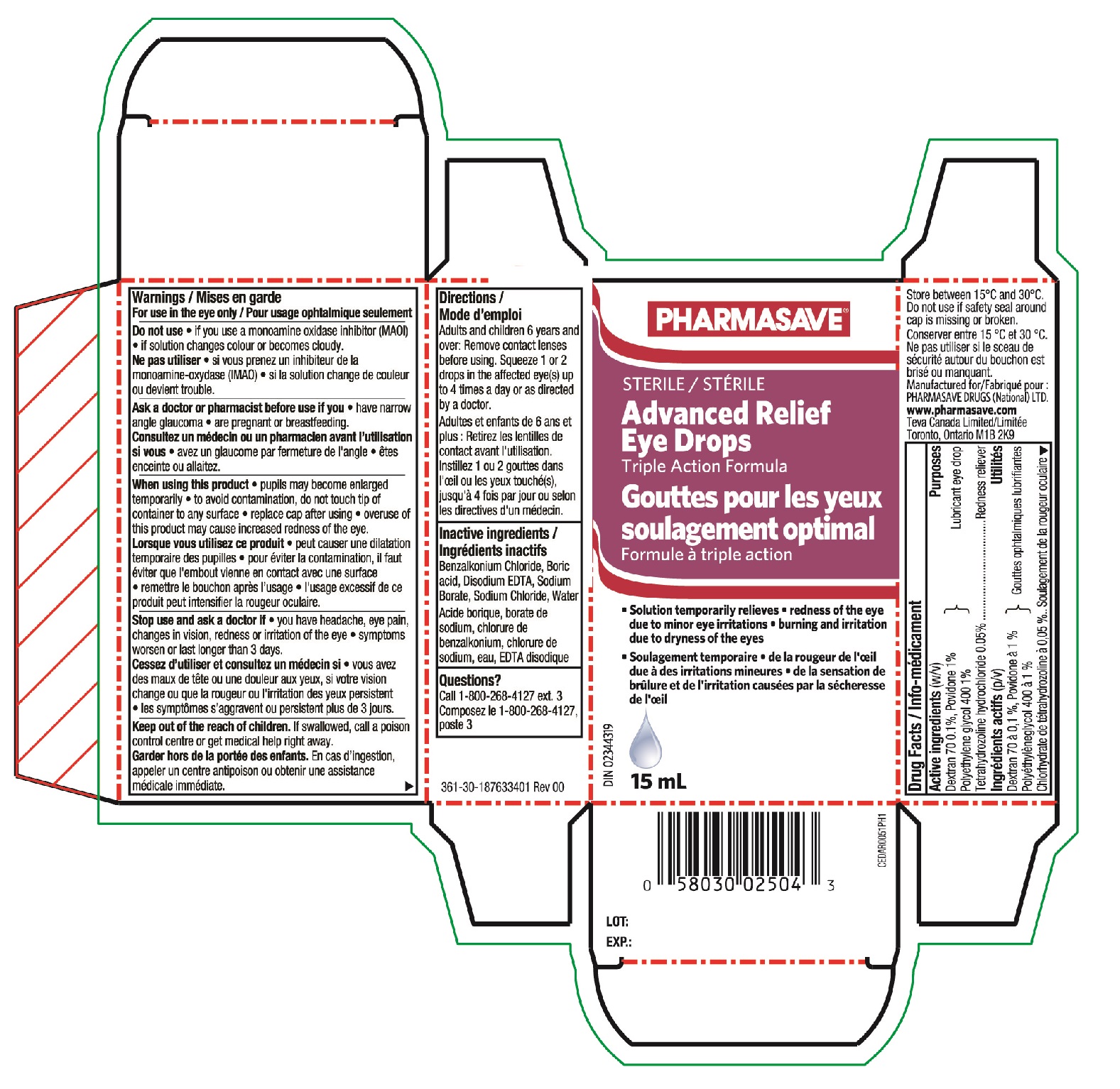 DRUG LABEL: Pharmasave Advanced Relief Eye Drops 15mL
NDC: 55651-990 | Form: SOLUTION/ DROPS
Manufacturer: KC Pharmaceuticals, Inc.
Category: otc | Type: HUMAN OTC DRUG LABEL
Date: 20251231

ACTIVE INGREDIENTS: DEXTRAN 70 0.1 g/100 mL; POVIDONE 1 g/100 mL; TETRAHYDROZOLINE HYDROCHLORIDE 0.05 g/100 mL; POLYETHYLENE GLYCOL 400 1 g/100 mL
INACTIVE INGREDIENTS: WATER; SODIUM CHLORIDE; BENZALKONIUM CHLORIDE; BORIC ACID; EDETATE DISODIUM ANHYDROUS; SODIUM BORATE

Pharmasave Advanced Relief Eye Drops 15mL (MFR- EXPORT)

Active ingredients

Dextran 70 0.1%

Povidone 1%

Polyethylene glycol 400 1%

Tetrahydrozoline hydrochloride 0.05%

Purposes

Lubricant eye drop

Redness reliever

Warnings

For use in the eye only

Do not use

- if you use a monoamine oxidase inhibitor (MAOI)
- if solution changes colour or becomes cloudy.

Ask a doctor or pharmacist before use if you

- have narrow angle glaucoma
- are pregnant or breastfeeding.

When using this product

- pupils may become enlarged temporarily
- to avoid contamination, do not touch tip of container to any surface
- replace cap after using
- overuse of this product may cause increased redness of the eye.

Stop use and ask a doctor if

- you have a headache, eye pain, changes in vision, redness or irritation of the eye
- symptoms worsen or last longer than 3 days.

Keep out of the reach of children.

If swallowed, call a poison control centre or get medical help right away.

Directions

Adults and children 6 years and over: Remove contact lenses before using. Squeeze 1 or 2 drops in the affected eye(s) up to 4 times a day or as directed by a doctor.

OTHER SAFETY INFORMATION

Store between 15°C and 30°C. Do not use if safety seal around cap is missing or broken.

Inactive ingredients

Benzalkonium Chloride, Boric acid, Disodium EDTA, Sodium Borate, Sodium Chloride, Water

Questions?

Call 1-800-268-4127 ext. 3